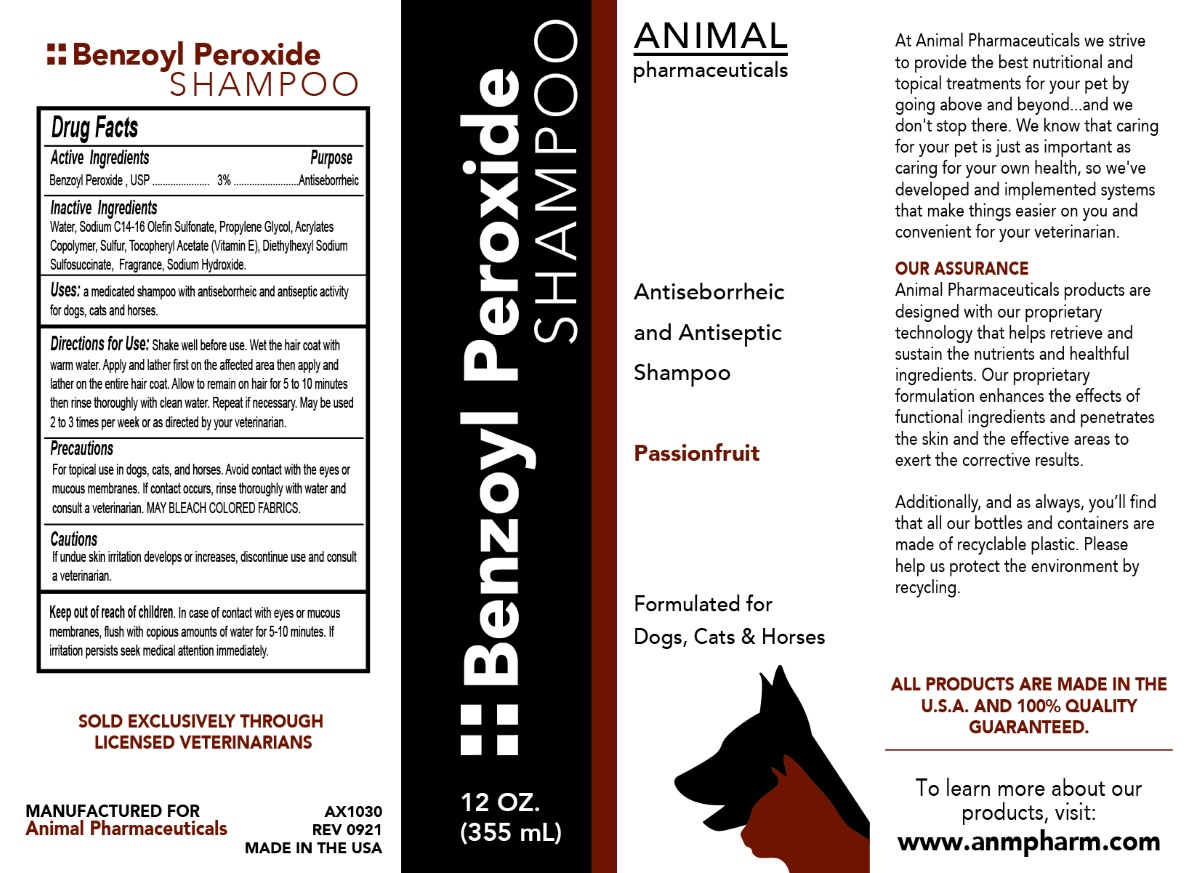 DRUG LABEL: Benzoyl Peroxide 3%
NDC: 68898-121 | Form: SHAMPOO
Manufacturer: Animal Pharmaceuticals
Category: animal | Type: OTC ANIMAL DRUG LABEL
Date: 20221121

ACTIVE INGREDIENTS: BENZOYL PEROXIDE 3 g/100 mL
INACTIVE INGREDIENTS: WATER; SODIUM C14-16 OLEFIN SULFONATE; PROPYLENE GLYCOL; BUTYL ACRYLATE/METHYL METHACRYLATE/METHACRYLIC ACID COPOLYMER (18000 MW); SULFUR; .ALPHA.-TOCOPHEROL ACETATE; DOCUSATE SODIUM; SODIUM HYDROXIDE

Benzoyl Peroxide SHAMPOO

Active Ingredients

Benzoyl Peroxide , USP 3%

Purpose

Antiseborrheic

Inactive Ingredients

Water, Sodium C14-16 Olefin Sulfonate, Propylene Glycol, Acrylates Copolymer, Sulfur, Tocopheryl Acetate (Vitamin E), Diethylhexyl Sodium Sulfosuccinate, Fragrance, Sodium Hydroxide.

Uses:

a medicated shampoo with antiseborrheic and antiseptic activity for dogs, cats and horses.

Directions for Use:

Shake well before use. Wet the hair coat with warm water. Apply and lather first on the affected area then apply and lather on the entire hair coat. Allow to remain on hair for 5 to 10 minutes then rinse thoroughly with clean water. Repeat if necessary. May be used 2 to 3 times per week or as directed by your veterinarian.

Precautions

For topical use in dogs, cats, and horses. Avoid contact with the eyes or mucous membranes. If contact occurs, rinse thoroughly with water and consult a veterinarian. MAY BLEACH COLORED FABRICS.

Cautions

If undue skin irritation develops or increases, discontinue use and consult a veterinarian.

Keep out of reach of children. In case of contact with eyes or mucous membranes, flush with copious amounts of water for 5-10 minutes. If irritation persists seek medical attention immediately.

Antiseborrheic and Antiseptic Shampoo

Passionfruit

Formulated for Dogs, Cats & Horses

At Animal Pharmaceuticals we strive to provide the best nutritional and topical treatments for your pet by going above and beyond....and we don't stop there. We know that caring for your pet is just as important as caring for your own health, so we've developed and implemented systems that make things easier on you and convenient for your veterinarian.

OUR ASSURANCE
Animal Pharmaceuticals products are designed with our proprietary technology that helps retrieve and sustain the nutrients and healthful ingredients. Our proprietary formulation enhances the effects of functional ingredients and penetrates the skin and the effective areas to exert the corrective results.

Additionally, and as always, you'll find that all our bottles and containers are made of recyclable plastic. Please help us protect the environment by recycling.

ALL PRODUCTS ARE MADE IN THE U.S.A. AND 100% QUALITY GUARANTEED.

To learn more about our products, visit:

www.anmpharm.com

SOLD EXCLUSIVELY THROUGH LICENSED VETERINARIANS

MANUFACTURED FOR
Animal Pharmaceuticals

MADE IN THE USA